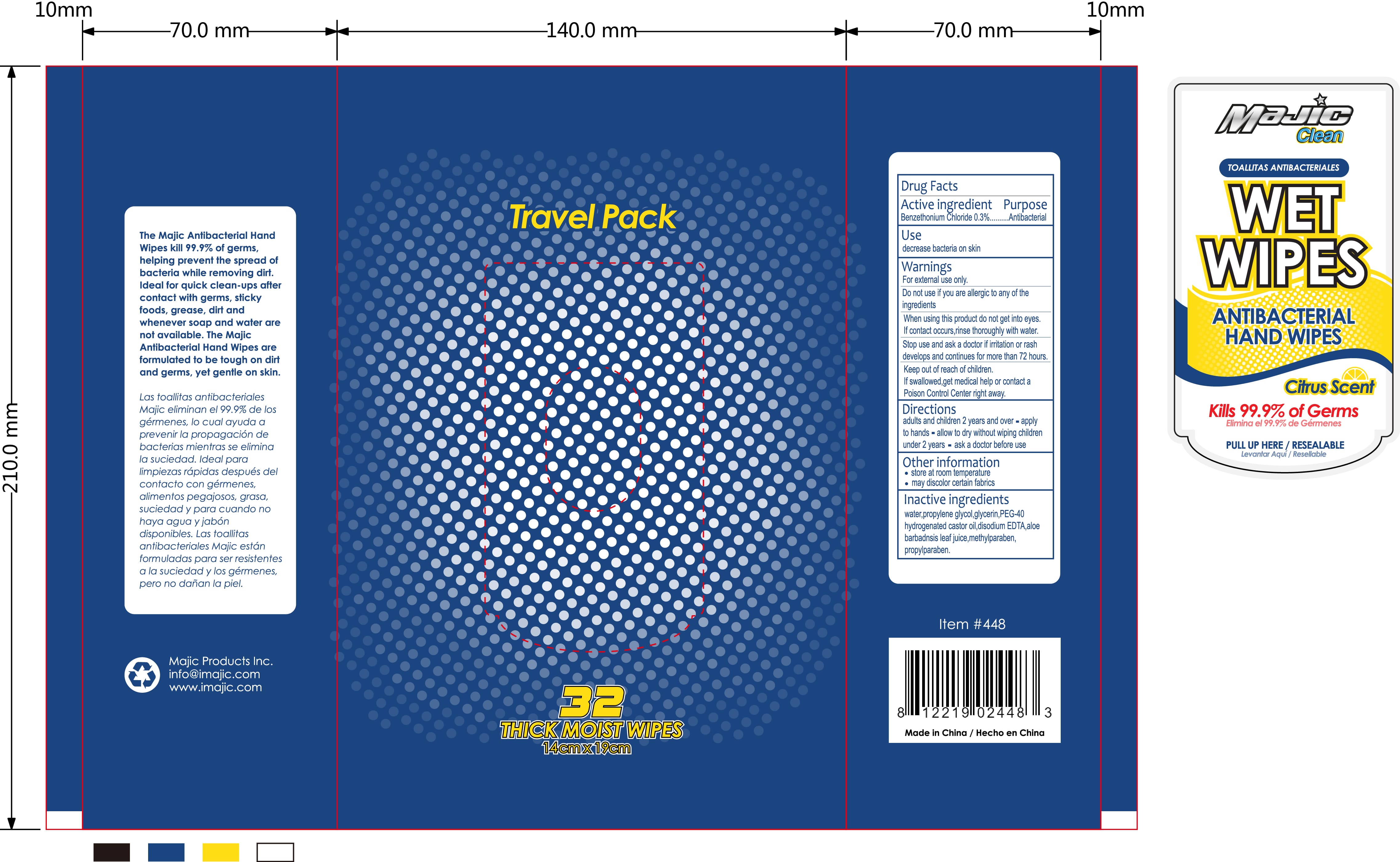 DRUG LABEL: Wet Wipes Antibacterial Hand Wipes
NDC: 78926-001 | Form: SWAB
Manufacturer: MAJIC PRODUCTS INC.
Category: otc | Type: HUMAN OTC DRUG LABEL
Date: 20200615

ACTIVE INGREDIENTS: BENZETHONIUM CHLORIDE 0.45 g/150 g
INACTIVE INGREDIENTS: EDETATE DISODIUM 0.0045 g/150 g; ALOE VERA LEAF 0.15 g/150 g; METHYLPARABEN 0.0165 g/150 g; PROPYLPARABEN 0.0045 g/150 g; WATER; POLYOXYL 40 HYDROGENATED CASTOR OIL 0.0045 g/150 g; GLYCERIN 0.15 g/150 g; PROPYLENE GLYCOL 0.15 g/150 g

Wet Wipes Antibacterial Hand Wipes

Active Ingredient

Benzethonium Chloride 0.3%

Purpose

Purpose Antimicrobial

Use

Decrease bacteria on skin

Warnings

For External use only

Do not use if you are allergic to any of the ingredients

When using this product do not get into eyes, if contact occurs rinse thoughly with water

Stop use and ask a doctor if irritation or rash develops and continues for more then 72 hours

Keep out of reach of children If swallowed, get medical help or contact a Poison Control Center

Directions

Adults and children 2 years and over

- apply to hands
- allow to dry without wiping
- Children under 2 years ask a doctor before use

Other Information

- store at room temperature
- may discolor certain fabrics

Inactive Ingredients

water, propylene gylcol, gylcerin, PEG-40 hydrogenated castor oil, disodium EDTA, aloe barbadnsis leaf juice, methylparaben, propylparaben

Package Label

32 wipes NDC 78926-001-01